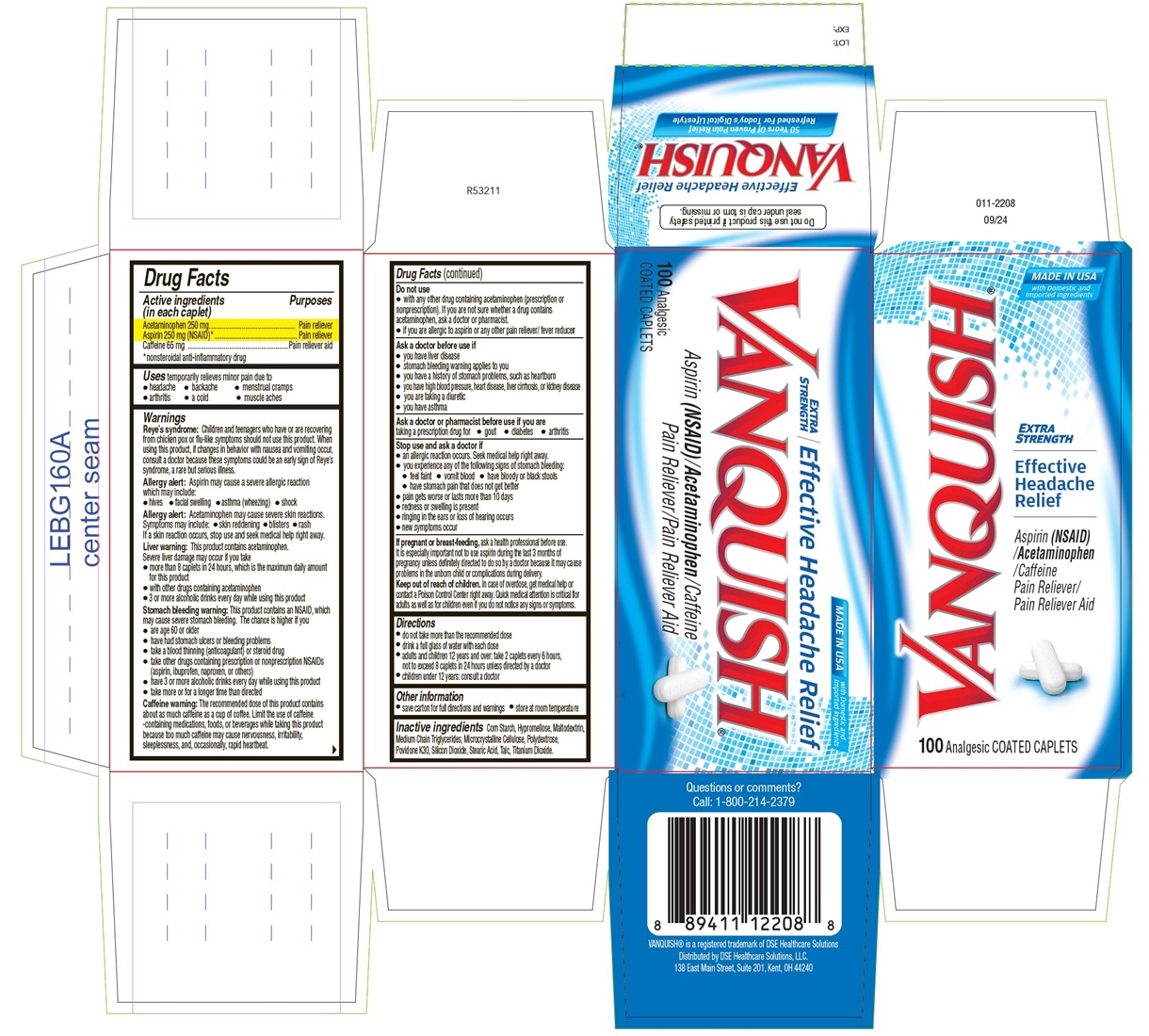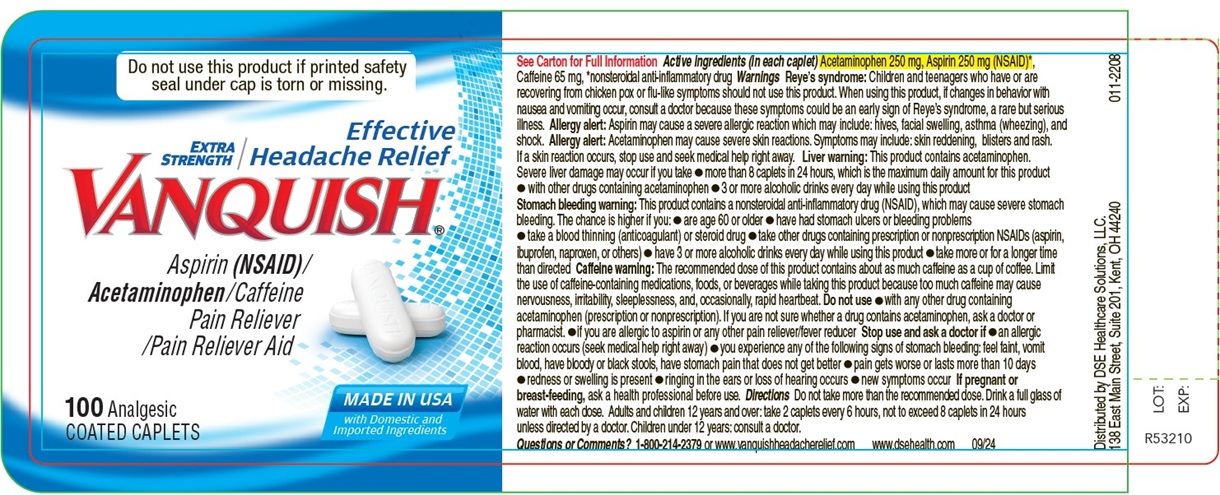 DRUG LABEL: Vanquish Extra Strength
NDC: 42364-2208 | Form: TABLET, COATED
Manufacturer: DSE Healthcare Solutions, LLC
Category: otc | Type: HUMAN OTC DRUG LABEL
Date: 20251215

ACTIVE INGREDIENTS: Acetaminophen 250 mg/1 1; Aspirin 250 mg/1 1; Caffeine 65 mg/1 1
INACTIVE INGREDIENTS: Starch, Corn; Hypromellose, Unspecified; Maltodextrin; Medium-Chain Triglycerides; Microcrystalline Cellulose; Polydextrose; Povidone K30; Silicon Dioxide; Stearic Acid; Talc; Titanium Dioxide

Vanquish Extra Strength
Drug Facts

ACTIVE INGREDIENT

PURPOSE

Active ingredients (in each caplet) | Purposes
Acetaminophen 250 mg | Pain reliever
Aspirin 250 mg (NSAID) [nonsteroidal anti-inflammatory drug] | Pain reliever
Caffeine 65 mg | Pain reliever aid

INDICATIONS AND USAGE

Uses temporarily relieves minor pain due to

- headache
- arthritis
- backache
- a cold
- menstrual cramps
- muscle aches

Warnings

Reye's syndrome: Children and teenagers who have or are recovering from chicken pox or flu-like symptoms should not use this product. When using this product, if changes in behavior with nausea and vomiting occur, consult a doctor because these symptoms could be an early sign of Reye's syndrome, a rare but serious illness.

Allergy alert: Aspirin may cause a severe allergic reaction which may include:

- hives
- facial swelling
- asthma (wheezing)
- shock

Allergy alert: Acetaminophen may cause severe skin reactions. Symptoms may include:

- skin reddening
- blisters
- rash

If a skin reaction occurs, stop use and seek medical help right away.

Liver warning: This product contains acetaminophen. Severe liver damage may occur if you take

- more than 8 caplets in 24 hours, which is the maximum daily amount for this product
- with other drugs containing acetaminophen
- 3 or more alcoholic drinks every day while using this product

Stomach bleeding warning: This product contains an NSAID, which may cause severe stomach bleeding. The chance is higher if you

- are age 60 or older
- have had stomach ulcers or bleeding problems
- take a blood thinning (anticoagulant) or steroid drug
- take other drugs containing prescription or nonprescription NSAIDs (aspirin, ibuprofen, naproxen, or others)
- have 3 or more alcoholic drinks every day while using this product
- take more or for a longer time than directed

Caffeine warning: The recommended dose of this product contains about as much caffeine as a cup of coffee. Limit the use of caffeine-containing medications, foods, or beverages while taking this product because too much caffeine may cause nervousness, irritability, sleeplessness, and, occasionally, rapid heartbeat.

Do not use

- with any other drug containing acetaminophen (prescription or nonprescription). If you are not sure whether a drug contains acetaminophen, ask a doctor or pharmacist.
- if you are allergic to aspirin or any other pain reliever/fever reducer

Ask a doctor before use if

- you have liver disease
- stomach bleeding warning applies to you
- you have a history of stomach problems, such as heartburn
- you have high blood pressure, heart disease, liver cirrhosis, or kidney disease
- you are taking a diuretic
- you have asthma

Ask a doctor or pharmacist before use if you are taking a prescription drug for

- gout
- diabetes
- arthritis

Stop use and ask a doctor if

- an allergic reaction occurs. Seek medical help right away.
- you experience any of the following signs of stomach bleeding:
  - feel faint
  - vomit blood
  - have bloody or black stools
  - have stomach pain that does not get better
- pain gets worse or lasts more than 10 days
- redness or swelling is present
- ringing in the ears or loss of hearing occurs
- new symptoms occur

PREGNANCY OR BREAST FEEDING

If pregnant or breast-feeding, ask a health professional before use. It is especially important not to use aspirin during the last 3 months of pregnancy unless definitely directed to do so by a doctor because it may cause problems in the unborn child or complications during delivery.

Keep out of reach of children. In case of overdose, get medical help or contact a Poison Control Center right away. Quick medical attention is critical for adults as well as for children even if you do not notice any signs or symptoms.

Directions

- do not take more than the recommended dose
- drink a full glass of water with each dose
- adults and children 12 years and over: take 2 caplets every 6 hours, not to exceed 8 caplets in 24 hours unless directed by a doctor
- children under 12 years: consult a doctor

Other information

- save carton for full directions and warnings
- store at room temperature

Inactive ingredients

Corn Starch, Hypromellose, Maltodextrin, Medium Chain Triglycerides, Microcrystalline Cellulose, Polydextrose, Povidone K30, Silicon Dioxide, Stearic Acid, Talc, Titanium Dioxide.

Questions or comments?

Call: 1-800-214-2379

VANQUISH® is a registered trademark of DSE Healthcare Solutions

Distributed by DSE Healthcare Solutions, LLC.
138 East Main Street, Suite 201, Kent, OH 44240

Principal Display Panel

MADE IN USA
with Domestic and Imported Ingredients
Extra
Strength
Effective Headache Relief
VANQUISH®
Aspirin (NSAID) / Acetaminophen / Caffeine
Pain Reliever / Pain Reliever Aid
100 Analgesic
COATED CAPLETS

Top Panel
Do not use this product if printed safety
seal under cap is torn or missing.
Effective Headache Relief
VANQUISH®50 Years of Proven Pain Relief
Refreshed for Today's Digital Lifestyle
LOT:
EXP:

Bottom Panel

Questions or comments?
Call: 1-800-214-2379
VANQUISH®is a registered trademark of DSE Healthcare Solutions
Distributed by DSE Healthcare Solutions, LLC.
138 East Main Street, Suite 201, Kent, OH 44240

R53211
011-2208
09/24

Do not use this product if printed safety
seal under cap is torn or missing.
See Carton for Full Information
Questions or Comments?
1-800-214-2379 or www.vanquishheadacherelief.com
www.dsehealth.com
09/24
R53210